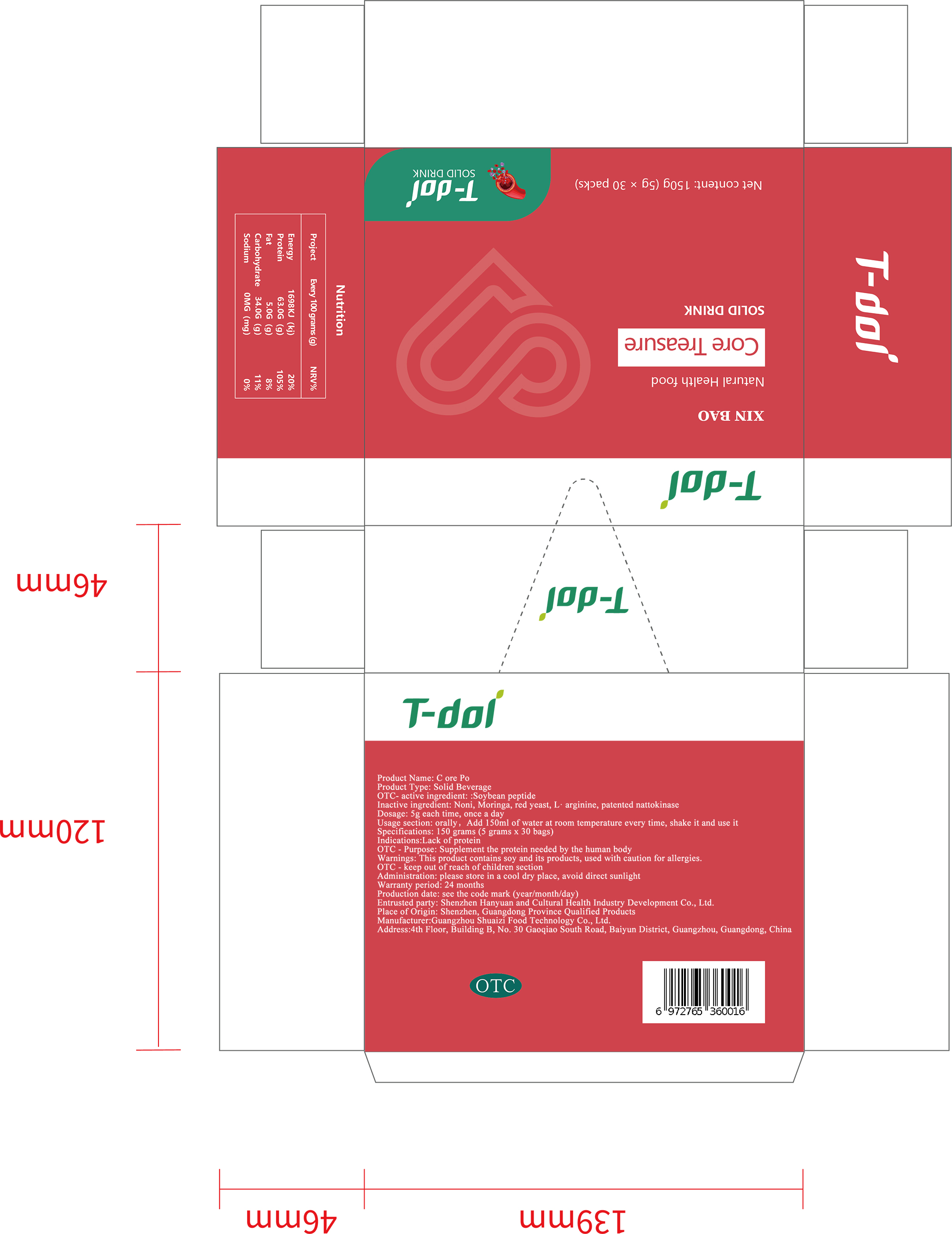 DRUG LABEL: T-dol XIN BAO
NDC: 75018-003 | Form: POWDER
Manufacturer: Shenzhen Hanyuanhe Cultural Health Industry Development Co., Ltd.
Category: homeopathic | Type: HUMAN OTC DRUG LABEL
Date: 20191103

ACTIVE INGREDIENTS: AMINO ACIDS, SOY 2 g/5 g
INACTIVE INGREDIENTS: NONI FRUIT 1 g/5 g; NATTOKINASE 0.2 g/5 g; RED YEAST 0.6 g/5 g; ARGININE 0.2 g/5 g; MORINGA OLEIFERA FRUIT 1 g/5 g

Inactive ingredient: Noni, Moringa, red yeast, L· arginine, patented nattokinase

Indications:Lack of protein
Usage section: orally, Add 150ml of water at room temperature every

OTC - keep out of reach of children section

PURPOSE

OTC - Purpose: Supplement the protein needed by the human body

OTC - active ingredient: :Soybean peptide

Dosage: 5g each time, once a day
Administration: please store in a cool dry place, avoid direct sunlight